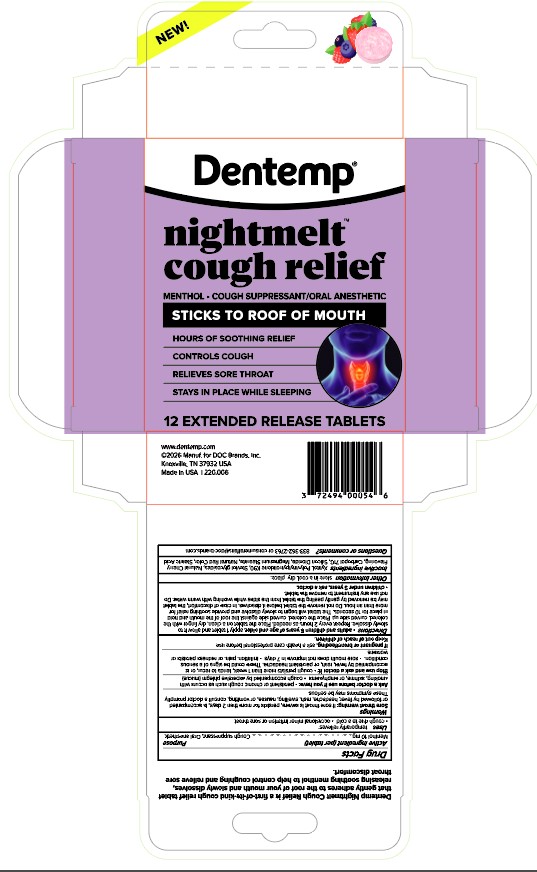 DRUG LABEL: Dentemp Nightmelt
NDC: 73653-220 | Form: TABLET, EXTENDED RELEASE
Manufacturer: DOC Brands
Category: otc | Type: HUMAN OTC DRUG LABEL
Date: 20260107

ACTIVE INGREDIENTS: MENTHOL 10 mg/1 1
INACTIVE INGREDIENTS: XYLITOL; STEARIC ACID; GLUCOSYL STEVIOL; POVIDONE K90; MALTODEXTRIN; CITRIC ACID; SILICON DIOXIDE; CHERRY; MAGNESIUM STEARATE; CARBOMER HOMOPOLYMER, UNSPECIFIED TYPE

ACTIVE INGREDIENT

Menthol 10mg

INACTIVE INGREDIENT

Xylitol, Polyvinylpyrrolidone K90, Steviol glycosides, Natural Cherry Flavoring, Carbopol 71G, Silicon Dioxide, Magnesium Stearate, Natural Red Color, Stearic Acid

Ask a doctor before use if you have: • persistent or chronic cough such as occurs with smoking, asthma, or emphysema • cough accompanied by excessive phlegm (mucus)

Stop use and ask a doctor if: • cough persists more than 1 week, tends to recur, or is accompanied by fever, rash, or persistent headache. These could be signs of a serious condition. • sore mouth does not improve in 7 days • irritation, pain, or redness persists or worsens

Questions or comments? 833-362-2763 or consumeraffairs@doc-brands.com

PREGNANCY OR BREAST FEEDING

If pregnant or breastfeeding, ask a health care professional before use. Keep out of reach of children

Keep out of reach of children.

WARNINGS

Sore throat warning: if sore throat is severe, persists for more than 2 days, is accompanied or followed by fever. headache, rash, swelling, nausea, or vomiting, consult a doctor promptly. These symptoms may be serious.

INSTRUCTIONS FOR USE

Directions • adults and children 5 years of age and older, apply 1 tablet and allow it to slowly dissolve. Repeat every 2 hours as needed. Place the tablet on a clean, dry finger with the colored, curved side up. Place the colored, curved side against the roof of the mouth and hold in place for 10 seconds. The tablet will begin to slowly dissolve and provide soothing relief for more than an hour. Do not remove the tablet before it dissolves. In case of discomfort, the tablet may be removed by gently peeling the tablet from the sides while washing with warm water. Do not use any instrument to remove the tablet.

PURPOSE

Purpose to aid as a cough suppressant and provide sore throat relief

INDICATIONS AND USAGE

For the temporary relief of cough due to minor throat irritaion and occasional minor sore throat

DOSAGE AND ADMINISTRATION

adults and children 5 years of age and older, apply 1 tablet and allow it to slowly dissolve. Repeat every 2 hours as needed up to 7 days.